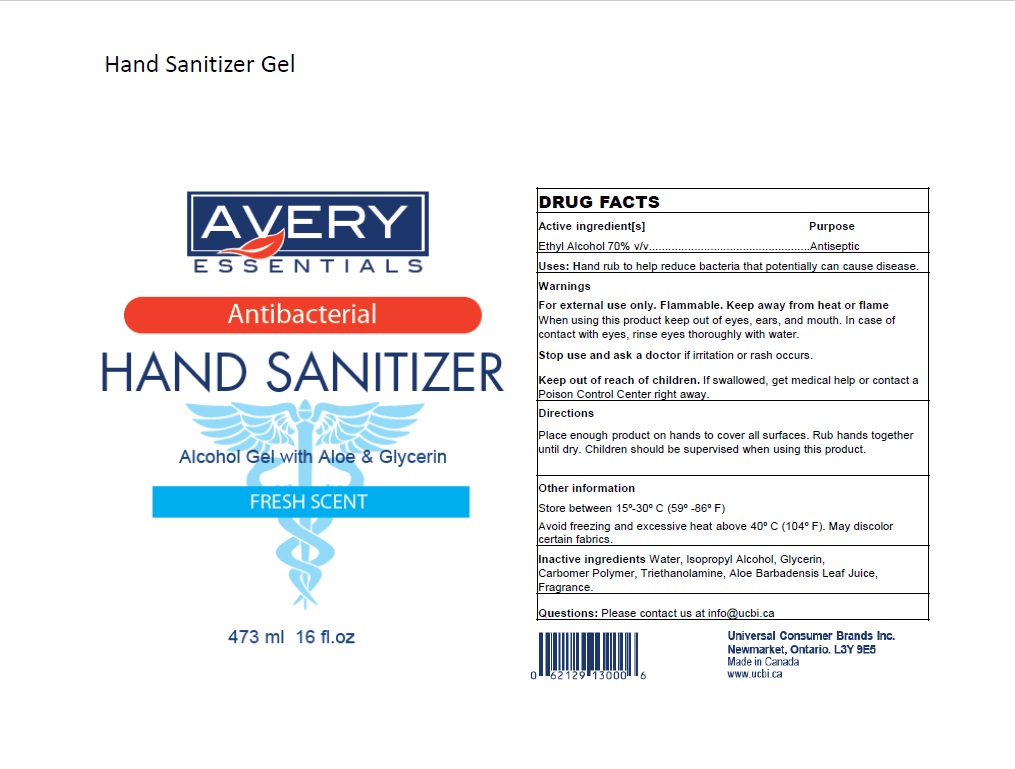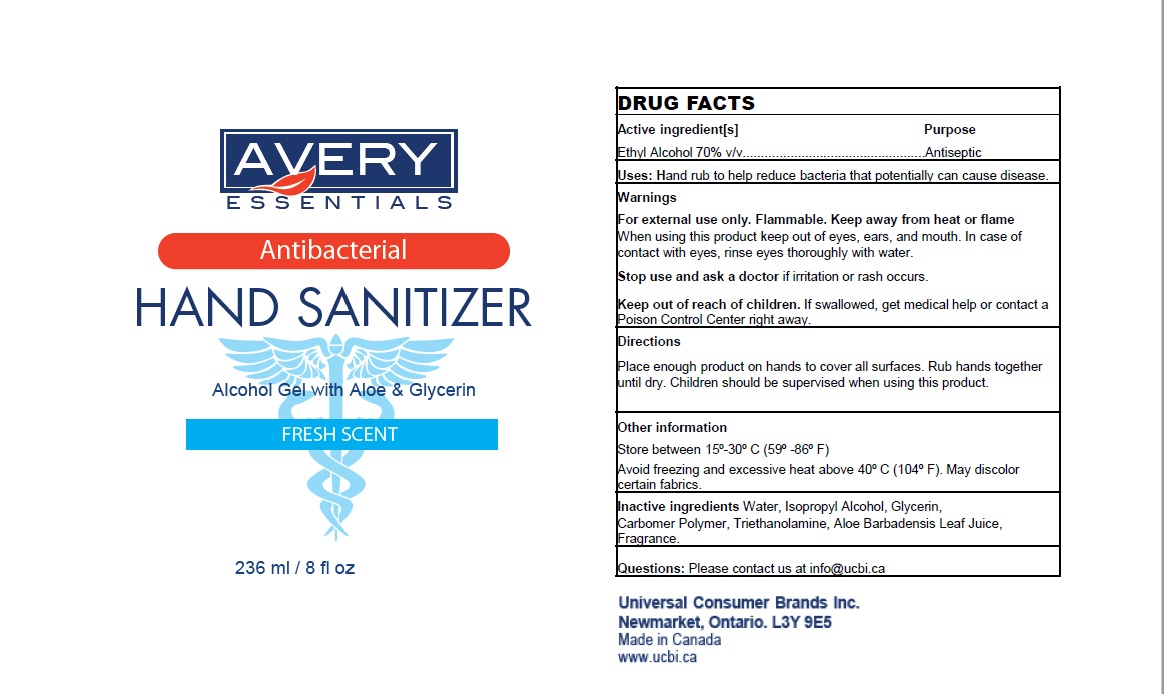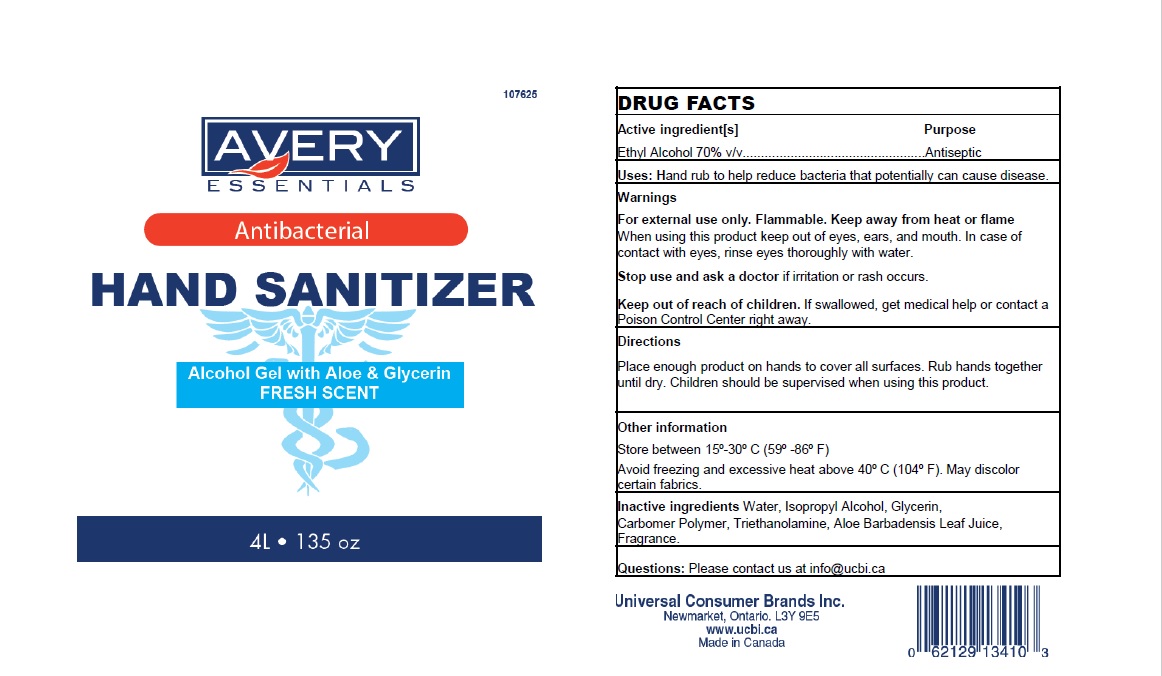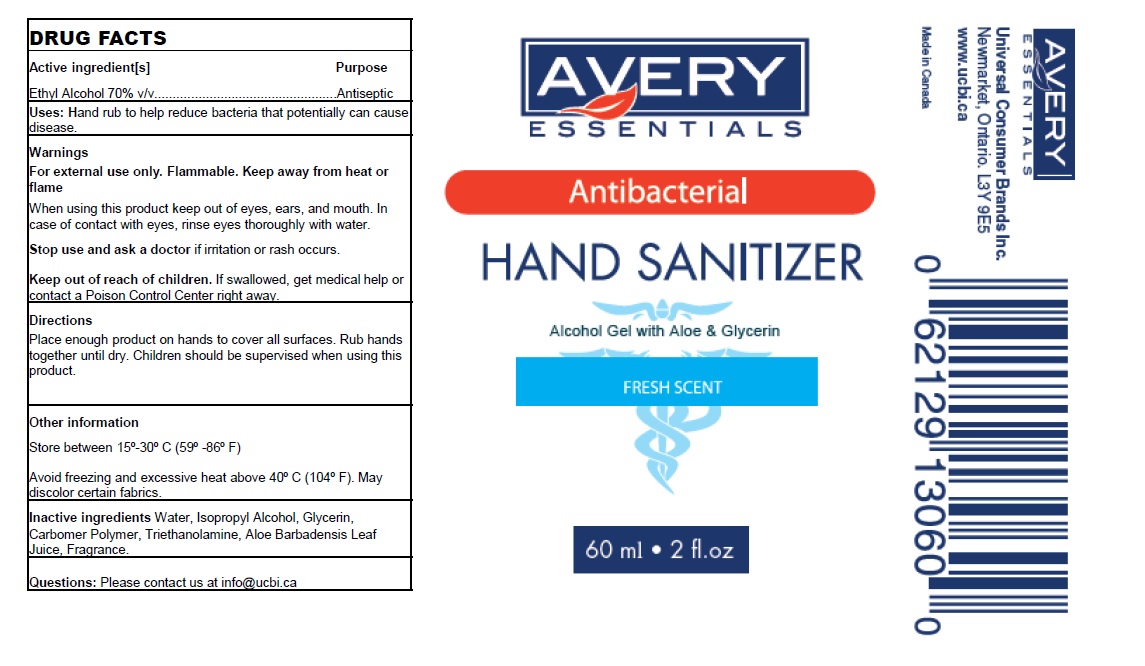 DRUG LABEL: Hand Sanitizer
NDC: 78489-002 | Form: GEL
Manufacturer: UNIVERSAL CONSUMER BRANDS INC
Category: otc | Type: HUMAN OTC DRUG LABEL
Date: 20200711

ACTIVE INGREDIENTS: ALCOHOL 70 mL/100 mL
INACTIVE INGREDIENTS: CARBOMER COPOLYMER TYPE A; GLYCERIN; TROLAMINE; ISOPROPYL ALCOHOL; ALOE; WATER

Avery Essentials Hand Sanitizer: Gel

Active Ingredient

Ethyl alcohol 70%.

Purpose

Antiseptic

INDICATIONS AND USAGE

For handwashing to decrease bacteria on the skin.

Warnings

Flammable, keep away from fire or flame. For external use only.

When using this product Avoid contact with eyes. In case of contact flush eyes with water.

Stop use and ask a doctor If redness or irritation develop and persist for more than 72 hours.

Keep out of reach of children. If swallowed get medical help or contact a Poison Control Center right away.

Directions

Spread on both hands, rub in, let dry.

INACTIVE INGREDIENT

Water, Isopropyl Alcohol, Glycerin, Aloe Barbadensis Leaf Juice, Fragrance.